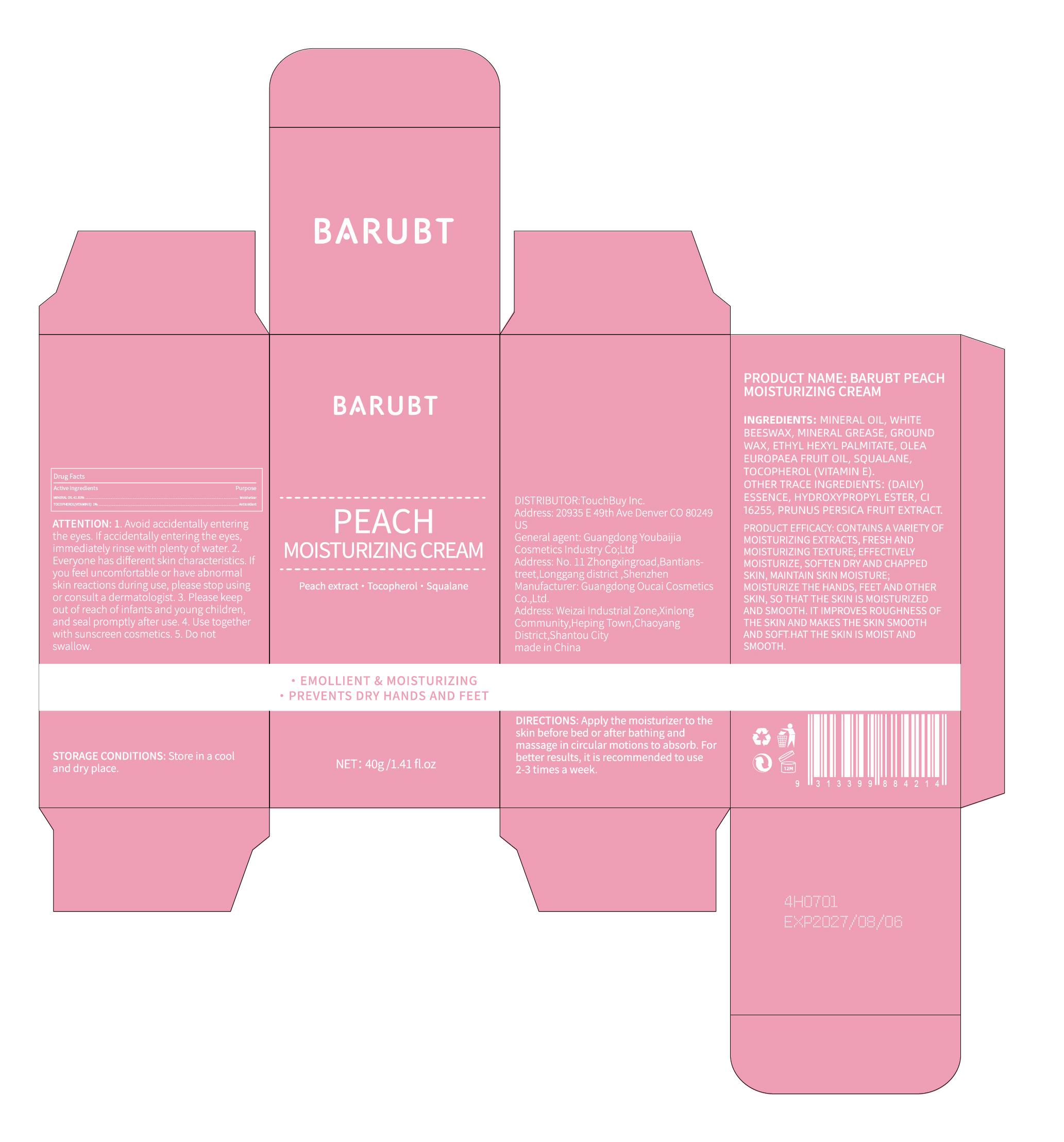 DRUG LABEL: BARUBT Peach Moisturizing Cream
NDC: 84712-021 | Form: CREAM
Manufacturer: Guangdong Youbaijia Cosmetic Industry Co., Ltd
Category: otc | Type: HUMAN OTC DRUG LABEL
Date: 20240918

ACTIVE INGREDIENTS: MINERAL OIL 16.732 g/40 g; TOCOPHEROL 0.4 g/40 g
INACTIVE INGREDIENTS: ETHYLHEXYL PALMITATE 4 g/40 g; OLEA EUROPAEA FRUIT VOLATILE OIL 4 g/40 g

ACTIVE INGREDIENT

MINERAL OIL 41.83%
TOCOPHEROL(VITAMIN E) 1%

INACTIVE INGREDIENT

WHITE BEESWAX

MINERAL GREASE

GROUND WAX

ETHYL HEXYL PALMITATE

OLEA EUROPAEA FRUIT OIL

SOUALANE

(DAILY)ESSENCE

HYDROXYPROPYL ESTER

CI 16255

PRUNUS PERSICA FRUIT EXTRACT

DO NOT USE

on damaged or broken skin

Keep away from children. Do not swallow.

PURPOSE

MOISTURIZING CREAM

QUESTIONS

Contact name: Jessie Peng
Company phone number: +1 818 579 7288
Company e-mail: jessie@registeragentllc.com

STOP USE

lf skin becomes red or irritated, discontinue use immediately and wash with water.

WHEN USING

keep out of eyes. Rinse with water to remove.

WARNINGS

For external use only.

STORAGE AND HANDLING

Keep away from light and in a dry place.

INDICATIONS AND USAGE

CONTAINS A VARIETY OF MOISTURIZING EXTRACTS, FRESH AND MOISTURIZING TEXTURE: EFFECTIVELY MOISTURIZE,SOFTEN DRY AND CHAPPED SKIN, MAINTAIN SKIN MOISTURE,MOISTURIZE THE HANDS, FEET AND OTHER SKIN, SO THAT THE SKIN IS MOISTURIZED AND SMOOTH.ITIMPROVES ROUGHNESS OF THE SKIN AND MAKES THE SKIN SMOOTH AND SOFT.HAT THE SKIN IS MOIST AND SMOOTH.

DOSAGE AND ADMINISTRATION

Apply the moisturizer to the skin before bed or after bathing and massage in circular motions to absorb. For better results, itis recommended to use 2-3 times a week.